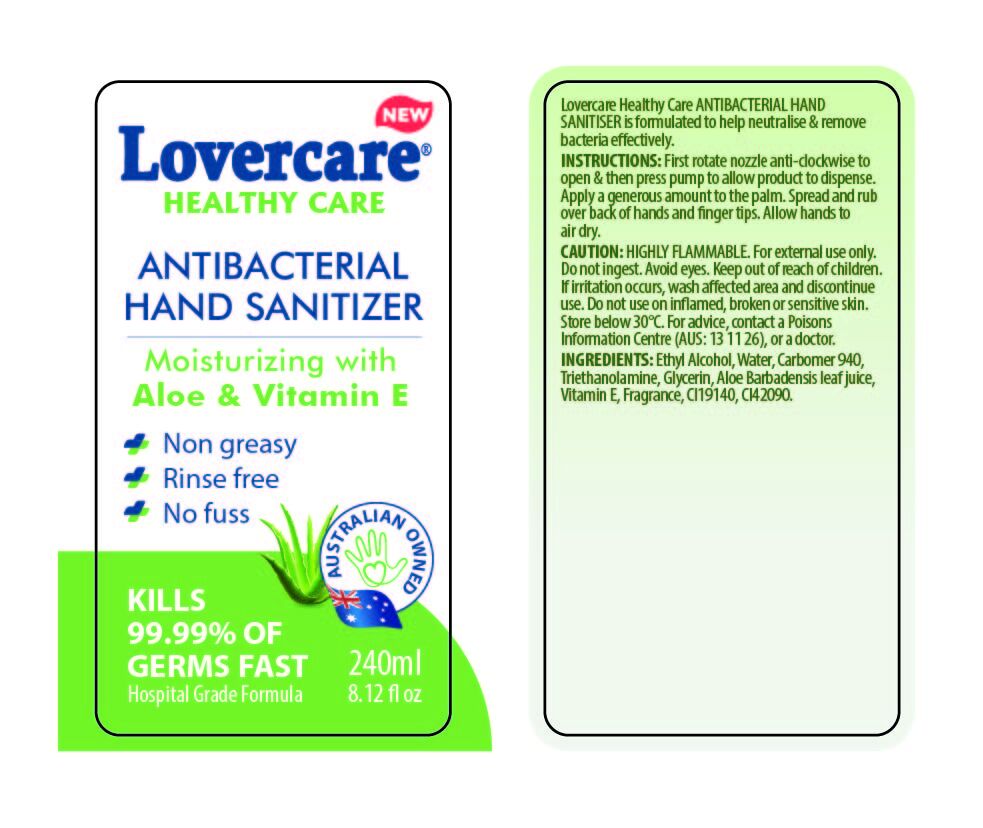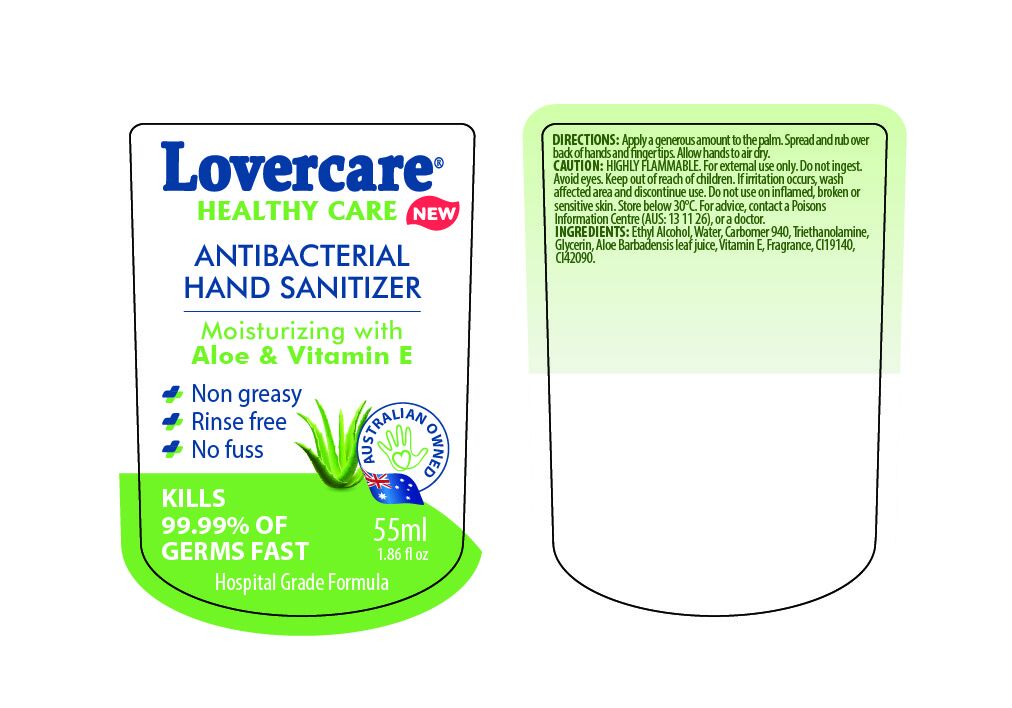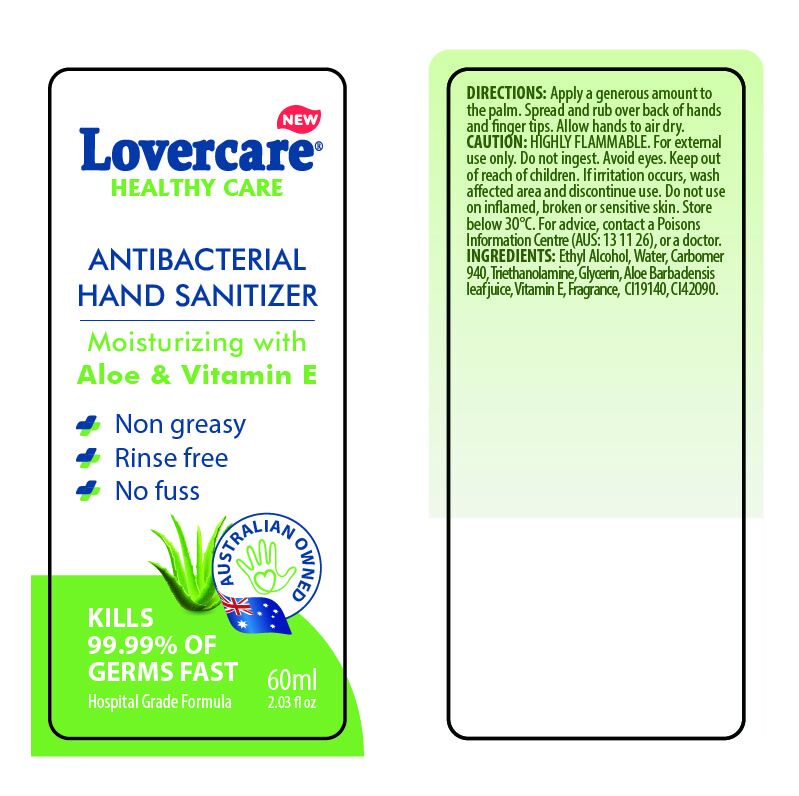 DRUG LABEL: HAND SANITIZER
NDC: 47993-288 | Form: GEL
Manufacturer: NINGBO JIANGBEI OCEAN STAR TRADING CO.,LTD
Category: otc | Type: HUMAN OTC DRUG LABEL
Date: 20201105

ACTIVE INGREDIENTS: ALCOHOL 70 g/112 mL
INACTIVE INGREDIENTS: WATER; CARBOMER 940; TRIETHANOLAMINE BENZOATE; GLYCERIN; ALOE VERA LEAF; TOCOPHEROL; FD&C YELLOW NO. 5; FD&C BLUE NO. 1

47993-288

Active ingredients

Ethyl Alcohol

PURPOSE

Antiseptic

INDICATIONS AND USAGE

Lovercare Healthy care ANTIBACTERIAL HAND SANITIZER is formulated to help neutralise & remove bacteria effectively.

DOSAGE AND ADMINISTRATION

INSTRUCTIONS:

First rotate nozzle anti-clockwise to open & then press pump to allow product to dispense. Apple a generous amount to the palm. Spread and rub over back of hands and finger tips. Allow hands to air dry.

WARNINGS

Caution:

Highly flammable. For external use only.

WHEN USING

Do not ingest. Avoid eyes.

Keep out of reach of children.

KEEP OUT OF REACH OF CHILDREN

If irrtation occurs, wash affected area and discontinue use.

Do not use on inflamed, broken or sensitive skin. Store below 30℃. For advice, contact a Poisons Information Centre (AUS: 13 11 26), or a doctor.

Inactive Ingredients:

Water,Carbomer 940,Triethanolamine,Glycerin,Aloe Barbadensis leaf juice,Vitamin E,Fragrance,CI19140,CI42090.